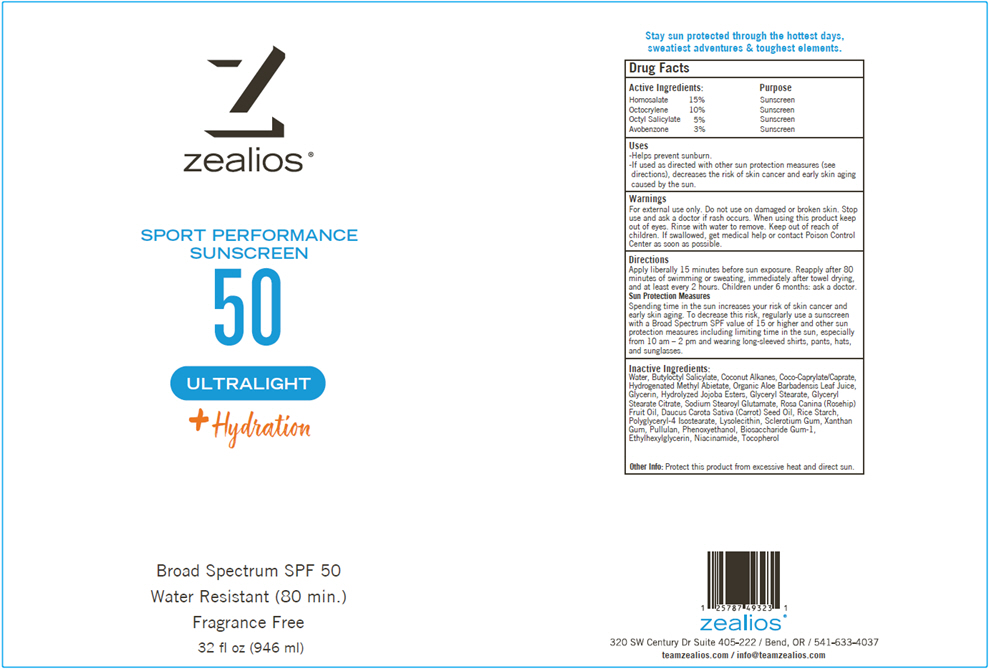 DRUG LABEL: Zealios Sport Performance Ultralight SPF 50 Sunscreen
NDC: 83326-003 | Form: CREAM
Manufacturer: Personal Best Products Inc. dba Zealios
Category: otc | Type: HUMAN OTC DRUG LABEL
Date: 20260203

ACTIVE INGREDIENTS: Homosalate 13200 mg/1 1; Octocrylene 8800 mg/1 1; OCTISALATE 4400 mg/1 1; Avobenzone 2640 mg/1 1
INACTIVE INGREDIENTS: Water; Butyloctyl Salicylate; Coconut Alkanes; COCOYL CAPRYLOCAPRATE; Hydrogenated Methyl Abietate; Glycerin; HYDROLYZED JOJOBA ESTERS (ACID FORM); GLYCERYL MONOSTEARATE; GLYCERYL STEARATE CITRATE; SODIUM STEAROYL GLUTAMATE; CARROT SEED OIL; STARCH, RICE; POLYGLYCERYL-4 ISOSTEARATE; BETASIZOFIRAN; Xanthan Gum; Pullulan; PHENOXYETHANOL; Biosaccharide Gum-1; Ethylhexylglycerin; Niacinamide; Tocopherol

Zealios® Sport Performance Ultralight SPF 50 Sunscreen

Drug Facts

ACTIVE INGREDIENT

Active Ingredients: |  |  | Purpose
Homosalate | 15% |  | Sunscreen
Octocrylene | 10% |  | Sunscreen
Octyl Salicylate | 5% |  | Sunscreen
Avobenzone | 3% |  | Sunscreen

Uses

- Helps prevent sunburn.
- If used as directed with other sun protection measures (see directions), decreases the risk of skin cancer and early skin aging caused by the sun.

Warnings

For external use only. Do not use on damaged or broken skin. Stop use and ask a doctor if rash occurs. When using this product keep out of eyes. Rinse with water to remove.

Keep out of reach of children. If swallowed, get medical help or contact Poison Control Center as soon as possible.

Directions

Apply liberally 15 minutes before sun exposure. Reapply after 80 minutes of swimming or sweating, immediately after towel drying, and at least every 2 hours. Children under 6 months: ask a doctor.

Sun Protection Measures

Spending time in the sun increases your risk of skin cancer and early skin aging. To decrease this risk, regularly use a sunscreen with a Broad Spectrum SPF value of 15 or higher and other sun protection measures including limiting time in the sun, especially from 10 am – 2 pm and wearing long-sleeved shirts, pants, hats, and sunglasses.

Inactive Ingredients

Water, Butyloctyl Salicylate, Coconut Alkanes, Coco-Caprylate/Caprate, Hydrogenated Methyl Abietate, Organic Aloe Barbadensis Leaf Juice, Glycerin, Hydrolyzed Jojoba Esters, Glyceryl Stearate, Glyceryl Stearate Citrate, Sodium Stearoyl Glutamate, Rosa Canina (Rosehip) Fruit Oil, Daucus Carota Sativa (Carrot) Seed Oil, Rice Starch, Polyglyceryl-4 Isostearate, Lysolecithin, Sclerotium Gum, Xanthan Gum, Pullulan, Phenoxyethanol, Biosaccharide Gum-1, Ethylhexylglycerin, Niacinamide, Tocopherol

Other Info

Protect this product from excessive heat and direct sun.

PRINCIPAL DISPLAY PANEL - 946 ml Bottle Label

zealios ®

SPORT PERFORMANCE
SUNSCREEN
50

ULTRALIGHT

^+ Hydration

Broad Spectrum SPF 50
Water Resistant (80 min.)
Fragrance Free

32 fl oz (946 ml)